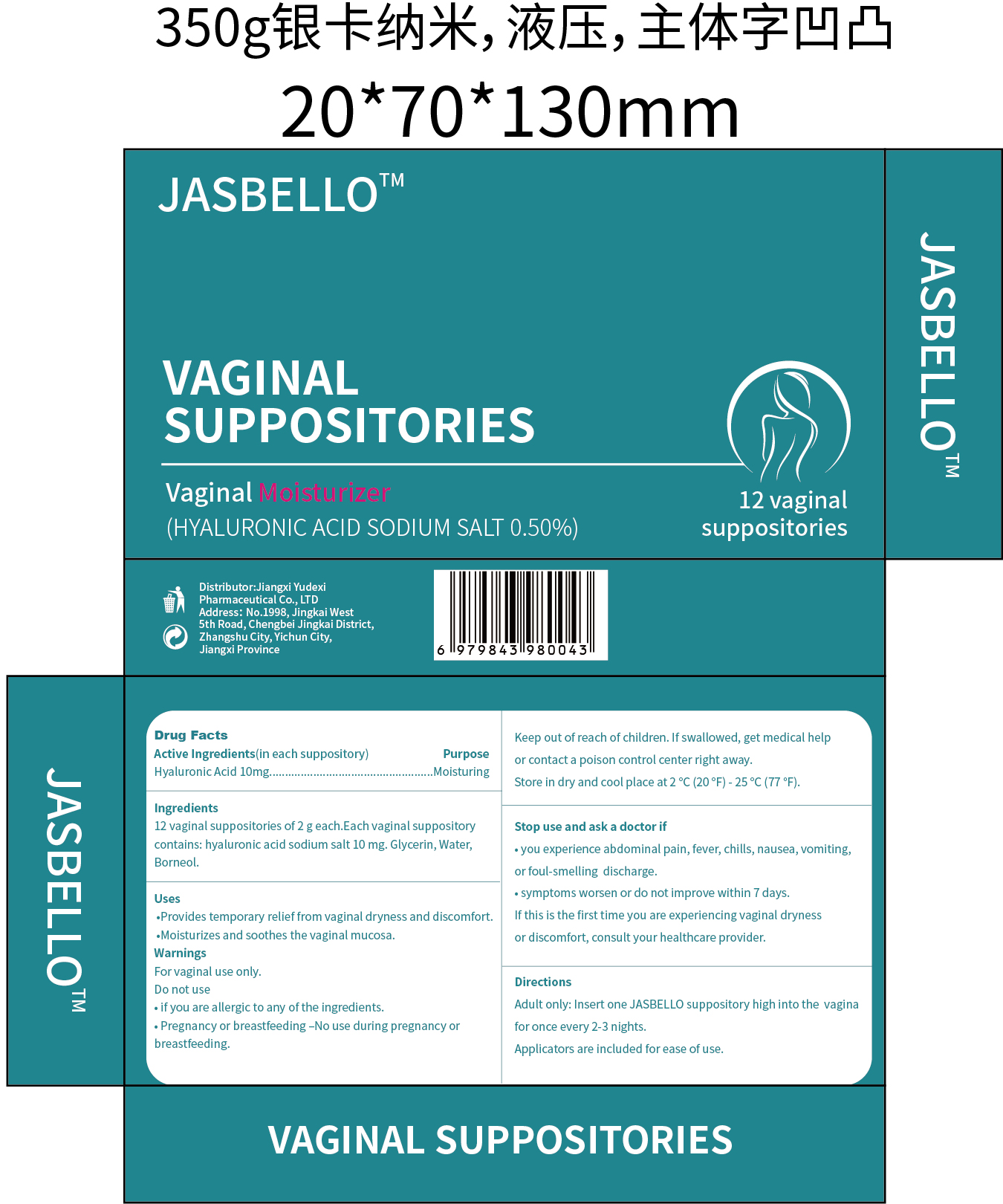 DRUG LABEL: JASBELLO VAGINAL
NDC: 85248-042 | Form: SUPPOSITORY
Manufacturer: Jiangxi Yudexi Pharmaceutical Co., LTD
Category: otc | Type: HUMAN OTC DRUG LABEL
Date: 20260202

ACTIVE INGREDIENTS: HYALURONIC ACID 10 mg/1 g
INACTIVE INGREDIENTS: BORNEOL; GLYCERIN; WATER

85248-042

Active Ingredient

Hyaluronic Acid 10mg

Purpose

Moisturing

Use

·Provides temporary relief from vaginal dryness and discomfort.· Molsturizes and soothes the vaginal mucosa.

Warnings

For vaginal use only.

Do not use

·if you are allergic to any of the ingredients.·Pregnancy or breastfeeding -No use during pregnancy or breastfeeding.

When Using

·Provides temporary relief from vaginal dryness and discomfort.· Molsturizes and soothes the vaginal mucosa.

Stop Use

·you experience abdominal pain, fever, chills, nausea, vomiting,or foul-smelling discharge.
·symptoms worsen or do not improve within7 days.If this is the first time you are experiencing vaginal dryness or discomfort, consult your healthcare provider.

Ask Doctor

·you experience abdominal pain, fever, chills, nausea, vomiting,or foul-smelling discharge.
·symptoms worsen or do not improve within7 days.If this is the first time you are experiencing vaginal dryness or discomfort, consult your healthcare provider.

Keep Oot Of Reach Of Children

Keep out of reach of children.lfswallowed, get medical helpor contact a poison control center right away.

Directions

Insert one JASBELLO suppository high into the vaginafor once every 2-3 nights.Applicators are included for ease of use.

Other information

Store in dry and coolplace at 2℃ (20°F)-25℃ (77°F).

Inactive ingredients

Glycerin,Water,Water